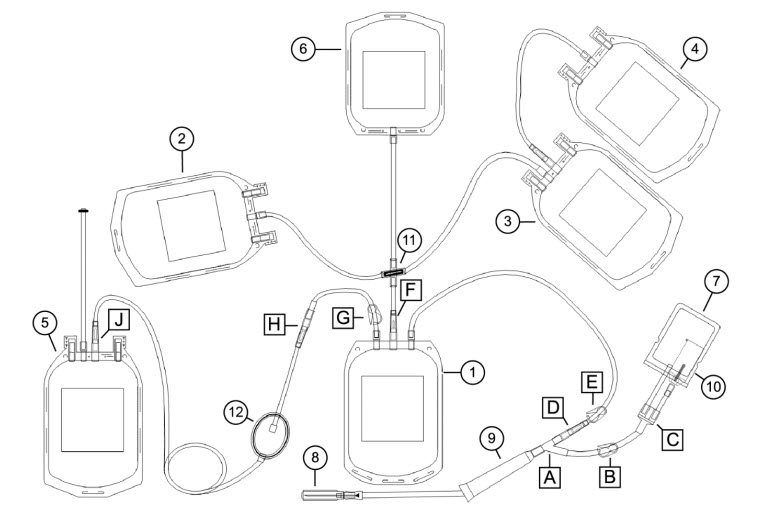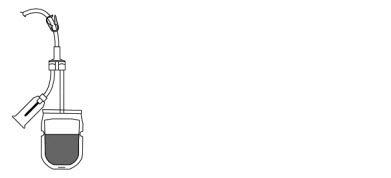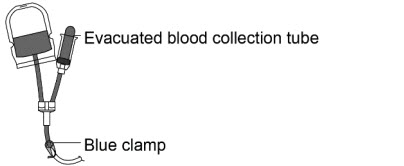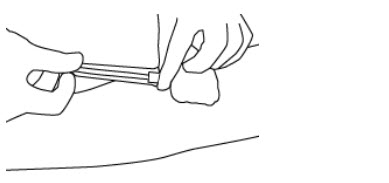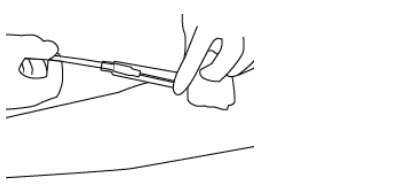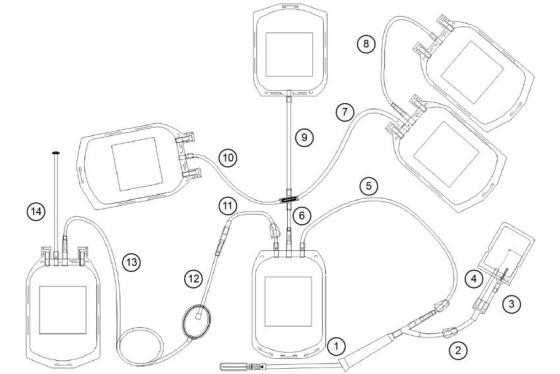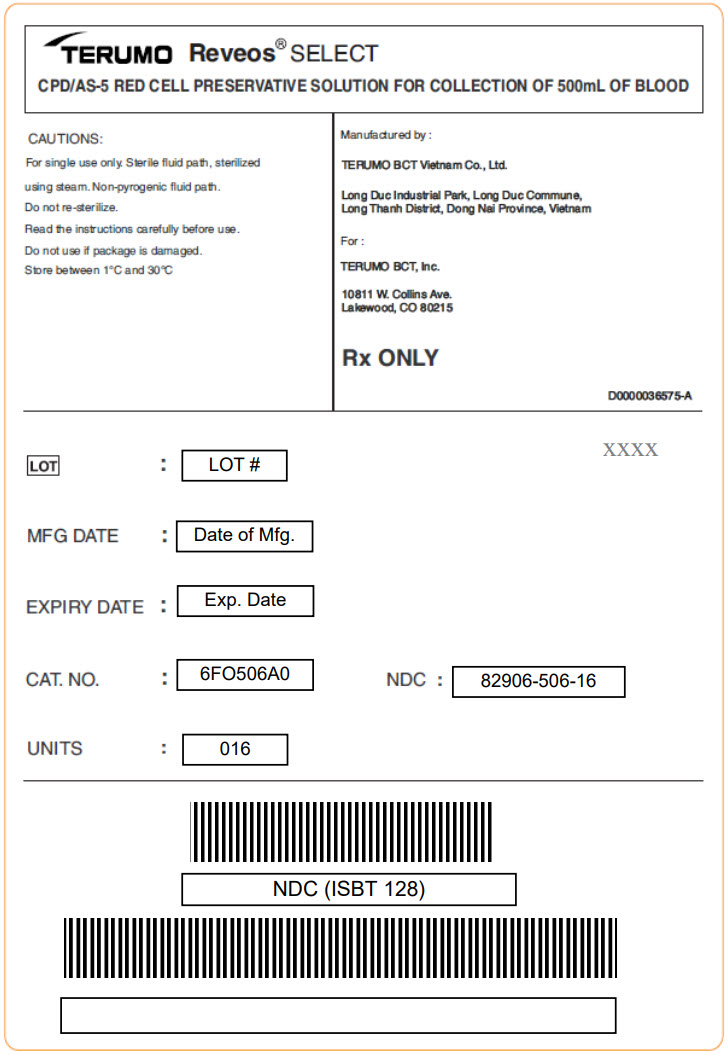 DRUG LABEL: Reveos Select CPD with AS-5 Red Cell Preservative Solution For Collection Of 500ml Of Blood
NDC: 82906-506 | Form: KIT | Route: INTRAVENOUS
Manufacturer: Terumo BCT Vietnam CO., Ltd.
Category: prescription | Type: HUMAN PRESCRIPTION DRUG LABEL
Date: 20250114

ACTIVE INGREDIENTS: Dextrose Monohydrate 1.624 g/70 mL; Trisodium Citrate Dihydrate 1.841 g/70 mL; Anhydrous Citric Acid 0.229 g/70 mL; Sodium Phosphate, Monobasic, Unspecified Form 0.176 g/70 mL; Anhydrous Dextrose 0.908 g/111 mL; Sodium Chloride 0.973 g/111 mL; Mannitol 0.583 g/111 mL; Adenine 0.035 g/111 mL
INACTIVE INGREDIENTS: Water; Water

HIGHLIGHTS OF PRESCRIBING INFORMATION

REVEOS® SELECT SET
CPD WITH AS-5 RED CELL PRESERVATIVE SOLUTION FOR COLLECTION OF 500 mL OF BLOOD
Terumo BCT, Inc.
HIGHLIGHTS OF PRESCRIBING INFORMATION These highlights do not include all the information needed to use the Reveos SELECT set safely and effectively. See full prescribing information for the Reveos SELECT set.
REVEOS SELECT SET
Sterile Fluid
PVC Plasticized With DEHP Bag
Initial U.S. Approval: TBD

1 INDICATIONS AND USAGE

- The Reveos® SELECT set is intended to collect a unit of whole blood and to process the whole blood unit on the Reveos Automated Blood Processing System, producing blood components. (1)
- Rx only. (1)

2 DOSAGE AND ADMINISTRATION

- Follow the instructions for collecting blood with the Reveos SELECT set. (2)
- Follow the instructions for post-processing and red blood cell leukoreduction with the Reveos SELECT set. (2)

3 DOSAGE FORMS AND STRENGTHS

- 70 mL Citrate Phosphate Dextrose (CPD) anticoagulant sterile fluid in a PVC plasticized with DEHP bag. (3)
- 111 mL Additive Solution 5 (AS-5) red cell preservative solution sterile fluid in a PVC plasticized with DEHP bag. (3)

4 CONTRAINDICATIONS

- None. (4)

5 WARNINGS AND PRECAUTIONS

- Do not reuse. (5)
- Inspect the packaging and the blood bag set prior to use. (5)
- The blood bag set is no longer sterile under certain conditions. (5)
- Do not process whole blood less than 2 hours after collection. (5)
- Residual leukocytes are not intended for transfusion. (5)
- Use aseptic technique during blood collection to ensure donor safety and product quality. (5)
- Do not vent the blood bag set. (5)

6. ADVERSE REACTIONS

To report SUSPECTED ADVERSE REACTIONS, contact Terumo BCT, Inc. at 1-877-339-4228 or FDA at 1-800-FDA-1088 or www.fda.gov/medwatch. (6)

8 USE IN SPECIFIC POPULATIONS

The Reveos SELECT set has not been studied in controlled clinical trials with specific populations. (8)

FULL PRESCRIBING INFORMATION

1 INDICATIONS AND USAGE

The Reveos® SELECT set is intended to collect a unit of whole blood and to process the whole blood unit on the Reveos Automated Blood Processing System, producing blood components.

Rx only.

2 DOSAGE AND ADMINISTRATION

Set Diagram

1 Whole blood bag | 7 Sample/diversion bag | A, C: Y connector
2 Interim platelet unit (IPU) bag | 8 Needle | B, G: Blue clamp
3 Plasma bag | 9 Needle injury protector (NIP) | D, F, H, J: CLIKTIP frangible connector
4 Plasma cryoprecipitate reduced bag | 10 Sample tube holder/luer adapter | E: White clamp
5 Red blood cell (RBC) bag | 11 Cross-connector
6 Residual leukocyte bag | 12 RBC leukoreduction filter

This document provides blood collection and post-processing instructions specific to the Reveos SELECT set. For warnings, cautions, and instructions on processing whole blood with the Reveos system, see the Reveos system operator's manual.

Note: Refer to the instructions for use provided by the manufacturer of your tubing sealer to ensure that the tubing sealer is appropriate for the tubing on the blood bag set.

Note: You must validate the process for producing, storing, and handling Cryoprecipitated Antihemophilic Factor within your institution's standard operating procedure (SOP), including procedures for using the plasma cryoprecipitate reduced bag.

Blood Collection

Required Supplies:

1. Scale and/or blood mixing device
2. Tubing sealer
3. Evacuated blood collection tubes
1. If it is part of your institution's SOP, make a loose knot in the collection tubing between white clamp E and the whole blood bag.
2. Separate the sample/diversion bag from the other bags.
3. Load the bags onto a scale and/or blood mixing device according to your institution's SOP. Ensure that the whole blood bag and the sample bag are lower than the donor's arm.
4. Close blue clamp B.
5. Apply a blood pressure cuff or a tourniquet to the donor's arm.
6. Prepare the venipuncture site.
7. Twist the needle cap until the resistance stops and then pull the needle cap straight off.
8. Perform the venipuncture according to your institution's SOP.
9. Open blue clamp B.
10. Position the sample/diversion bag with blue clamp B at the top and the sample tube holder/luer adapter at the bottom (see Figure 1). Allow the desired volume of whole blood to flow into the sample/diversion bag. The nominal volume of the sample bag is 60 mL. When the volume reaches the marking, approximately 40 mL has been collected.
11. Close blue clamp B.
12. Break CLIKTIP D to allow the whole blood to flow into the whole blood bag. Bend the CLIKTIP in both directions to ensure that you break it completely.
13. Seal the sample/diversion tubing as near as possible to Y connector A. Seal the tubing according to your institution's SOP.
14. Invert the sample/diversion bag and transfer donor blood samples from the sample/diversion bag, using evacuated blood collection tubes. Transfer samples as soon as possible after venipuncture to avoid possible clot formation in the sample/diversion bag.
  a. Hold the sample/diversion bag and sample tube holder/luer adapter in one hand with blue clamp B positioned at the bottom (see Figure 2).
  b. Using the other hand, insert a blood collection tube firmly into the sample tube holder/luer adapter. After filling the blood collection tube, remove the tube from the sample tube holder. Repeat the process to take additional samples.
15. Mix the whole blood and the anticoagulant during collection according to your institution's SOP.
16. Collect the target volume of blood ± 10%, as specified on the whole blood bag label.
17. Close white clamp E and perform one of the following steps:
  - If you made a knot in the collection tubing in step 1, tighten the knot firmly.
  - If you did not make a knot in step 1, seal the collection tubing near CLIKTIP D.
18. Hold the needle hub and then slide the NIP partially over the needle hub (see Figure 3).
19. Gently pull on the tubing to withdraw the needle from the donor's arm and into the NIP until the needle locks securely (see Figure 4).
20. Seal the collection tubing near CLIKTIP D if you did not do so in step 17. Disconnect the sealed tubing that includes the needle and the sampling assembly. Dispose of the needle, the NIP, and the sample tube holder safely according to your institution's SOP and/or local regulations.
21. Immediately after collection is complete, invert the whole blood bag several times to thoroughly mix the whole blood and the anticoagulant.
22. If required, strip the blood in the collection tubing into the whole blood bag according to your institution's SOP.
23. Seal and disconnect the collection tubing between 1 in and 2 in (2.5 cm and 5.0 cm) away from the whole blood bag. Dispose of the collection tubing safely according to your institution's SOP and/or local regulations.
24. Place the whole blood unit into a temperature-controlled environment according to your institution's SOP.
25. Pack and transport the whole blood unit to the processing laboratory according to your institution's SOP.

Figure 1: Sample/diversion bag

Figure 2: Collecting a whole blood sample

Figure 3: Sliding the NIP over the needle hub

Figure 4: Withdrawing the needle into the NIP

Post-Processing and Red Blood Cell Leukoreduction

Required Supplies:

1. Leukoreduction rack
2. Tubing sealer
1. After processing, remove the plasma bag, the plasma cryoprecipitate reduced bag, the residual leukocyte bag, and the IPU bag from the organizer and handle them according to your institution's SOP.
  Note: You must rest and agitate the IPU prior to platelet pooling. For conditions for resting and agitating the IPU, see the platelet pooling set instructions for use.
2. Prepare a leukoreduction rack with a head height of at least 43½ in (110 cm).
3. Remove the RBC bag from the organizer.
4. Hang the RBC bag from the leukoreduction rack so that the filter hangs vertically.
5. Open blue clamp G.
6. Break CLIKTIP H.
7. Break CLIKTIP J.
8. Drain all of the additive solution through the filter and into the whole blood bag.
9. Close blue clamp G.
10. Gently mix the additive solution with the RBC unit in the whole blood bag.
11. Hang the whole blood bag on the leukoreduction rack.
12. Ensure that the tubing is free of kinks or other obstructions.
13. Open blue clamp G and allow the mixture of red blood cells and additive solution to flow through the leukoreduction filter.
  Do not squeeze the whole blood bag to increase the draining rate. Filtration is complete when the inlet side of the leukoreduction filter collapses and the red blood cells drain from the inlet side of the filter.
14. Seal the RBC tubing below the leukoreduction filter and disconnect the RBC bag. Ensure that the filter remains in a vertical position while you seal the tubing, as this prevents the loss of red blood cells.
15. Dispose of the whole blood bag and filter assembly safely according to your institution's SOP and/or local regulations.
16. Seal the line for sampling segments according to your institution's SOP.
17. Store the RBC product according to your institution's SOP.

Parenteral drug products should be inspected visually for particulate matter and discoloration prior to administration, whenever the solution and container permit.

3 DOSAGE FORMS AND STRENGTHS

70 mL Citrate Phosphate Dextrose (CPD) anticoagulant is a sterile solution in a PVC plasticized with DEHP bag. Each 70 mL of CPD contains: Dextrose (anhydrous) 1.624 g, Trisodium Citrate (dihydrate) 1.841 g, Citric Acid (monohydrate) 0.229 g, Sodium Dihydrogen Phosphate (dihydrate) 0.176 g, and water for injection up to 70 mL.

111 mL Additive Solution 5 (AS-5) red cell preservative solution is a sterile solution in a PVC plasticized with DEHP bag. Each 111 mL of AS-5 contains: Dextrose (anhydrous) 0.908 g, Sodium Chloride 0.973 g, Mannitol 0.583 g, Adenine 0.035 g, and water for injection up to 111 mL.

4 CONTRAINDICATIONS

None.

5 WARNINGS AND PRECAUTIONS

- Single-use product. Do not reuse. This product is intended to be single use only and is not intended to be reused or re-sterilized in any manner. Terumo Blood and Cell Technologies cannot ensure the functionality or sterility of the product if it is reused or re-sterilized. Reuse of a single-use disposable set may result in:
  - Product performance issues due to loss of product integrity, including but not limited to the following:
    - Fluid leaks
    - Parts that are warped or deformed
    - Plastics that are brittle and discolored
    - Filters that have reduced filtration capabilities
  - Viral infections such as hepatitis or human immunodeficiency virus (HIV)
  - Bacterial infections
  - Cross-contamination
  Any of these risks could result in serious injury or death. These risks are shared by product users, donors, patients, and recipients of the end product of the device.
- Inspect the packaging and the blood bag set prior to use. Do not use the set if any of the following conditions are present:
  - There are tears or holes in the outer aluminum foil packaging or in the individual transparent packaging wrap.
  - The tubing has severe kinks.
  - The blood bag set is incorrectly assembled.
  - The blood bag set is defective or damaged, or there are any leaks from the fluid-filled components of the set.
  - Any clamps are closed.
  - The needle cap is not in place.
  - The solutions are cloudy or discolored or contain particulates.
  Using the blood bag set under these conditions may result in product contamination or poor performance during collection and/or processing.
  Note: It is normal to have some condensation in the outer aluminum foil pouch and individual transparent packaging wrap due to sterilization.
- The blood bag set is no longer sterile if any of the following conditions occur:
  - You disconnect the sample/diversion bag before you seal the sample/diversion tubing.
  - You remove blood samples before you seal the sample/diversion tubing.
  - The integrity of the set is compromised for any reason.
  Manage the blood bag set according to your institution's SOP.
- Do not process whole blood less than 2 hours after collection. Processing blood too soon after collection may result in incomplete RBC leukoreduction and/or a reduced platelet yield.
- Residual leukocytes are a by-product of the processing procedure and contain mostly white blood cells (WBC), with some plasma, platelets, and red blood cells (RBC). Residual leukocytes are not intended for transfusion.
- Use aseptic technique during blood collection to ensure donor safety and product quality.
- Do not vent the blood bag set.

6. ADVERSE REACTIONS

To report SUSPECTED ADVERSE REACTIONS, contact Terumo BCT, Inc. at 1-877-339-4228 or FDA at 1-800-FDA-1088 or www.fda.gov/medwatch.

8 USE IN SPECIFIC POPULATIONS

The Reveos SELECT set has not been adequately studied in controlled clinical trials with specific populations.

11 DESCRIPTION

The Reveos SELECT set has been evaluated for use with the Reveos system.

The blood and fluid pathways of the blood bag set are steam-sterilized and are non-pyrogenic.

The blood bag set is intended for use by appropriately trained phlebotomists who collect whole blood and by blood center personnel who process whole blood using the Reveos system.

The formulas of the active ingredients are provided in Tables 1 and 2.

Table 1: CPD Active Ingredients
Ingredients | Molecular Formula | Molecular Weight
Dextrose (anhydrous) | C6H12O6 | 180.16 g/mol
Trisodium Citrate (dihydrate) | C6H5Na3O72H2O | 294.10 g/mol
Citric Acid (monohydrate) | C6H8O7H2O | 210.14 g/mol
Sodium Dihydrogen Phosphate (dihydrate) | NaH2PO42H2O | 156.01 g/mol
Water for Injection | H2O | 18.02 g/mol

Each 70 mL of CPD contains: Dextrose (anhydrous) 1.624 g, Trisodium Citrate (dihydrate) 1.841 g, Citric Acid (monohydrate) 0.229 g, Sodium Dihydrogen Phosphate (dihydrate) 0.176 g, and water for injection up to 70 mL.

Table 2: AS-5 Active Ingredients
Ingredients | Molecular Formula | Molecular Weight
Dextrose (anhydrous) | C6H12O6 | 180.16 g/ mol
Sodium Chloride | NaCl | 58.44 g/mol
Mannitol | C6H14O6 | 182.17 g/mol
Adenine | C5H5N5 | 135.13 g/mol
Water for injection | H2O | 18.02 g/mol

Each 111 mL of AS-5 contains: Dextrose (anhydrous) 0.908 g, Sodium Chloride 0.973 g, Mannitol 0.583 g, Adenine 0.035 g, and water for injection up to 111 mL.

The PVC plasticized with DEHP bags are not made with natural rubber latex.

The bags contain materials that have been tested to demonstrate the suitability of the containers for storing pharmaceutical solutions. The bags are nontoxic and biologically inert. The blood bag set is a closed system and is not dependent upon entry of external air during administration. The blood bag set is overwrapped to provide protection from the physical environment and to provide an additional moisture barrier when necessary.

12 CLINICAL PHARMACOLOGY

12.1. Mechanism of Action

CPD Mechanism of Action

CITRATE PHOSPHATE DEXTROSE acts as an extracorporeal anticoagulant by binding the free calcium in the blood. Calcium is a necessary co-factor to several steps in the clotting cascade. The following ingredients are key components of the solution:

- Citric Acid for pH regulation
- Sodium Citrate functions as an anticoagulant
- Dextrose for isotonicity
- Sodium Dihydrogen Phosphate for pH buffering

This solution has no clinical effect in transfused patients.

AS-5 Mechanism of Action

ADDITIVE SOLUTION FORMULA 5 acts to preserve and extend the shelf life of packed RBC products for later transfusion to patients. The following ingredients are key components of the solution:

- Dextrose for RBC nutrition
- Sodium Chloride for isotonicity
- Mannitol to protect RBC membranes
- Adenine to support adenosine triphosphate (ATP) levels

This solution has no clinical effect in transfused patients.

16 HOW SUPPLIED/STORAGE AND HANDLING

The blood bag sets are packaged in outer aluminum foil pouches. Each outer aluminum foil pouch contains 2 blood bag sets. Each case contains 8 outer aluminum foil pouches.

CATALOG NUMBER | NDC NUMBER
6FO506A0 | Carton: | 82906-506-16
 | Aluminum foil: | 82906-506-02
 | Primary Collect Bag: | 82906-506-01

STORAGE

- Long-term storage temperature: 1 °C to 30 °C
- Permitted temperature excursions:
  - –20 °C to 1 °C for up to 2 weeks
  - Up to 50 °C for up to 1 week

Use blood bag sets within 28 days after you open the outer aluminum foil pouch. To store unused blood bag sets, return them to the outer aluminum foil pouch and reclose the pouch with tape or a clip. Once you open the transparent packing wrap, you must use the blood bag set within 7 days, not exceeding 28 days from when you opened the outer aluminum foil pouch. Each outer aluminum foil pouch contains sachets that absorb oxygen. Dispose of the sachets and the outer aluminum foil pouch with normal waste.

Issued: February 2023

Manufactured by:
TERUMO BCT Vietnam CO., Ltd.
Long Duc Industrial Park, Long Duc Commune,
Long Thanh District, Dong Nai Province, Vietnam

For:
Terumo BCT, Inc.
10811 W. Collins Ave.
Lakewood, CO 80215

RETURN OF USED PRODUCT

If for any reason this product must be returned to Terumo BCT, Inc., a returned goods authorization (an RGA number) is required from Terumo BCT prior to shipping. Instructions for cleaning and materials, including appropriate shipping containers, proper labeling, and an RGA number, may be obtained from the Terumo BCT Quality Assurance Department. IT IS THE RESPONSIBILITY OF THE HEALTH CARE INSTITUTION TO ADEQUATELY PREPARE AND IDENTIFY THE PRODUCT FOR RETURN SHIPMENT. Please contact your local representative for information regarding returned goods and product complaints.

Tubing Specifications (non-sterile, nominal [Note: The tubing dimensions listed on this document are nominal values and are intended for use in determining compatibility with various types of laboratory equipment. The nominal values are specified target dimensions; however, because they are based on non‑sterile tubing measurements, and due to variations in the manufacturing process, the actual dimensions may be slightly different.] dimensions)
 |  | Description | Primary tubing | Sample tube holder/luer adapter tubing
 |  | Item(s) | 1, 2, 4, 5, 6, 7, 8, 9, 10, 11, 12, 13, 14 | 3
 |  | Wall Thickness | 0.7 mm | 1.3 mm
 |  | Outer Diameter | 4.4 mm | 4.4 mm
 |  | Inner Diameter | 3.0 mm | 1.8 mm

Tubing Set Composition

- Primary tubing: Polyvinyl chloride (PVC) plasticized with Di(2-ethylhexyl)phthalate (DEHP)
- Bags: PVC plasticized with DEHP
- RBC leukoreduction filter: PVC plasticized with DEHP housing, polybutylterephthalate media
- Access needle: Stainless steel (contains cobalt)
- Needle injury protector (NIP): Polypropylene (PP)
- Sample tube holder/luer adapter: PVC/polycarbonate housing, stainless steel needle
- Clamps: Polyacetal
- Cross-connector: PVC

Not made with natural rubber latex.

This product may be covered by one or more patents or pending patent applications.

See TERUMOBCT.COM/patents for details.

Terumo BCT, Inc. ("Terumo Blood and Cell Technologies", "Terumo BCT")

PRINCIPAL DISPLAY PANEL - 70 mL Bag Pouch Case Label

TERUMO Reveos® SELECT

CPD/AS-5 RED CELL PRESERVATIVE SOLUTION FOR COLLECTION OF 500mL OF BLOOD

CAUTIONS:

For single use only. Sterile fluid path, sterilized
using steam. Non-pyrogenic fluid path.

Do not re-sterilize.

Read the instructions carefully before use.

Do not use if package is damaged.

Store between 1°C and 30°C

Manufactured by :

TERUMO BCT Vietnam Co., Ltd.

Long Duc Industrial Park, Long Duc Commune,
Long Thanh District, Dong Nai Province, Vietnam

For :

TERUMO BCT, Inc.

10811 W. Collins ave.
Lakewood, CO 80215

Rx ONLY

D0000036575-A

XXXX

LOT : LOT #

MFG DATE : Date of Mfg.

EXPIRY DATE : Exp. Date

CAT. NO. : 6FO506A0

UNITS : 016

NDC : 82906-506-16

NDC (ISBT 128)